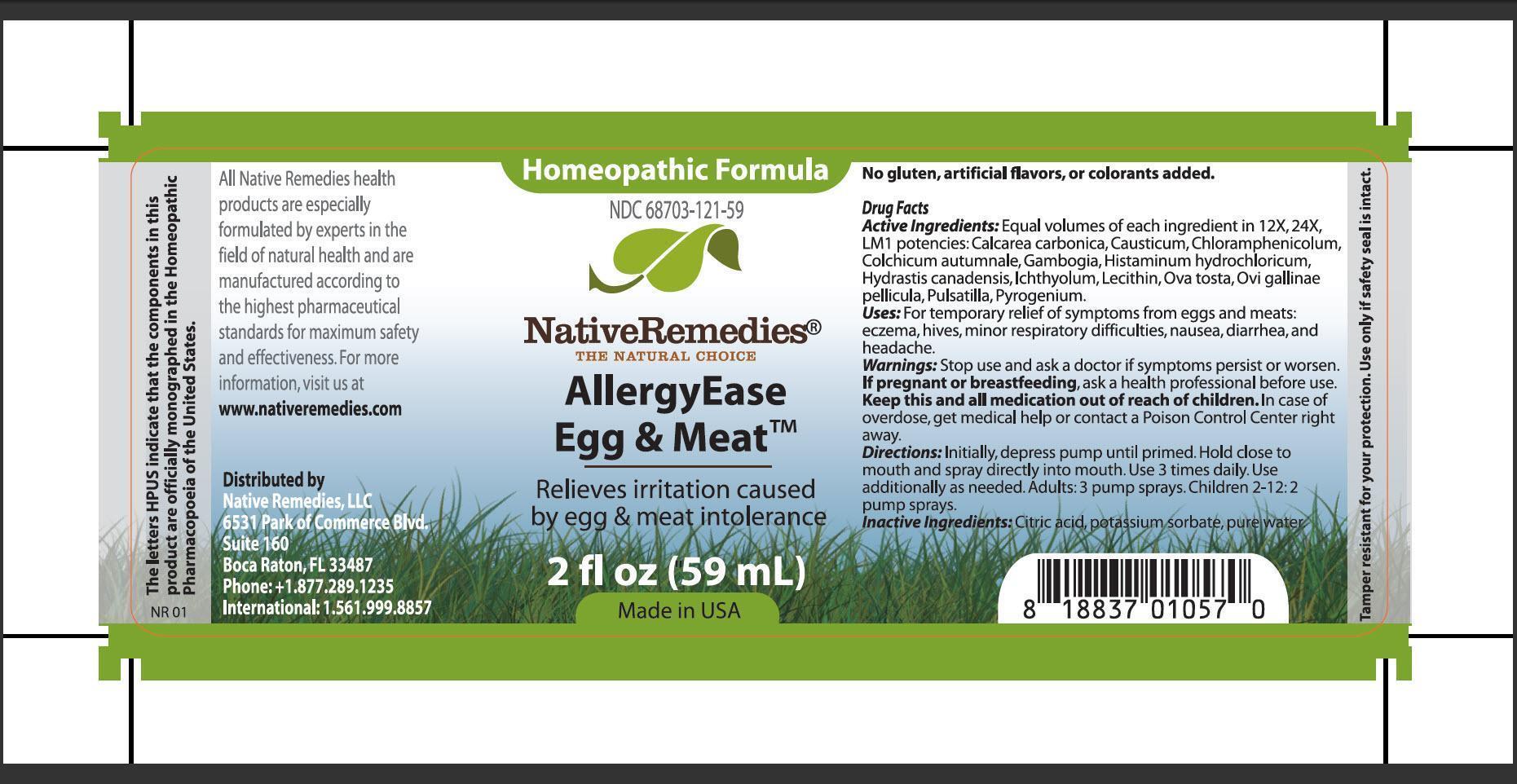 DRUG LABEL: AllergyEase Egg and Meat
NDC: 68703-121 | Form: SPRAY
Manufacturer: Native Remedies, LLC
Category: homeopathic | Type: HUMAN OTC DRUG LABEL
Date: 20130626

ACTIVE INGREDIENTS: OYSTER SHELL CALCIUM CARBONATE, CRUDE 12 [hp_X]/59 mL; CAUSTICUM 12 [hp_X]/59 mL; CHLORAMPHENICOL 12 [hp_X]/59 mL; COLCHICUM AUTUMNALE BULB 12 [hp_X]/59 mL; GAMBOGE  12 [hp_X]/59 mL; HISTAMINE DIHYDROCHLORIDE 12 [hp_X]/59 mL; GOLDENSEAL 12 [hp_X]/59 mL; ICHTHAMMOL 12 [hp_X]/59 mL; EGG PHOSPHOLIPIDS 12 [hp_X]/59 mL; EGG SHELL, COOKED 12 [hp_X]/59 mL; EGG SHELL MEMBRANE 12 [hp_X]/59 mL; PULSATILLA VULGARIS 12 [hp_X]/59 mL; RANCID BEEF 12 [hp_X]/59 mL
INACTIVE INGREDIENTS: CITRIC ACID MONOHYDRATE; POTASSIUM SORBATE; WATER

AllergyEase Egg and Meat

PURPOSE

Relieves irritation caused by egg and meat intolerance

Drug Facts
Active Ingredients: Equal volumes of each ingredient in 12X, 24X, LM1 potencies: Calcarea carbonica, Causticum, Chloramphenicolum, Colchicum autumnale, Gambogia, Histaminum hydrochloricum, Hydrastis canadensis, Ichthyolum, Lecithin, Ova tosta, Ovi gallinae pellicula, Pulsatilla, Pyrogenium

INDICATIONS AND USAGE

Uses: For temporarily relief of symptoms from eggs and meats: eczema, hives, minor respiratory difficulties, nausea, diarrhea, and headache

WARNINGS

Warnings: Stop use and ask a doctor if symptoms persist or worsen

PREGNANCY OR BREAST FEEDING

If pregnant or breastfeeding, ask a health professional before use

KEEP OUT OF REACH OF CHILDREN

Keep this and all medication out of reach of children

OVERDOSAGE

In case of overdose, get medical help pr contact a Poison Control Center right away

DOSAGE AND ADMINISTRATION

Directions: Initially, depress pump until primed. Hold close to mouth and spray directly into mouth. Use 3 times daily. Use additionally as needed. Adults: 3 pump sprays. Children 2-12: 2 pump sprays

Inactive Ingredients: Citric acid, potassium sorbate, pure water

PATIENT COUNSELING INFORMATION

The letter HPUS indicate that the components in this product are officially monographed in the Homeopathic Pharmacopoeia of the United States.

All Native Remedies products are especially formulated by experts in the field of natural health and are manufactured according to the highest pharmaceutical standards for maximum safety and effectiveness. For more information, visit us at www.nativeremedies.com

Distributed by
Native Remedies, LLC
6531 Park of Commerce Blvd.
Suite 160
Boca Raton, Fl 33487
Phone:+1.877.289.1235
International:1.561.999.8857

No gluten, artificial flavors, or colorants added

STORAGE AND HANDLING

Tamper resistant for your protection. Use only if safety seal is intact